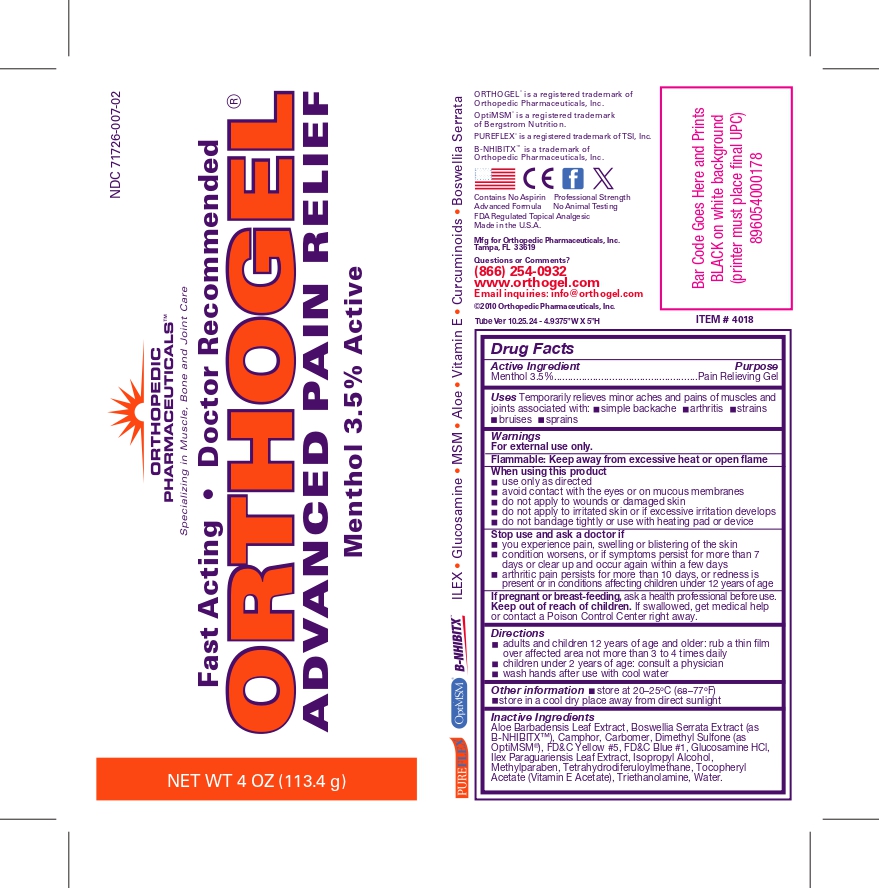 DRUG LABEL: ORTHOGEL Menthol 3.5%
NDC: 71726-007 | Form: GEL
Manufacturer: LiquidCapsule Manufacturing LLC
Category: otc | Type: HUMAN OTC DRUG LABEL
Date: 20250709

ACTIVE INGREDIENTS: MENTHOL 3.5 g/100 g
INACTIVE INGREDIENTS: ALOE VERA LEAF; INDIAN FRANKINCENSE; CAMPHOR (SYNTHETIC); CARBOMER HOMOPOLYMER, UNSPECIFIED TYPE; DIMETHYL SULFONE; FD&C YELLOW NO. 5; FD&C BLUE NO. 1; GLUCOSAMINE HYDROCHLORIDE; ILEX PARAGUARIENSIS LEAF; ISOPROPYL ALCOHOL; TETRAHYDRODIFERULOYLMETHANE; .ALPHA.-TOCOPHEROL ACETATE; TROLAMINE; Water

ORTHOGEL Menthol 3.5%

Active Ingredient

Menthol 3.5%

Purpose

Pain Relieving Gel

Uses

Temporarily relieves minor aches and pains of muscles and joints associated with:

- simple backache
- arthritis
- strains
- bruises
- sprains

Warnings

For external use only.

Flammable: Keep away from excessive heat or open flame

When using this product:

- use only as directed
- avoid contact with the eyes or on mucous membranes
- do not apply to wounds or damaged skin
- do not apply to irritated skin or if excessive irritation develops
- do not bandage tightly or use with heating pad or device

Stop use and ask a doctor if

- you experience pain, swelling or blistering of the skin
- condition worsens, or if symptoms persist for more than 7 days or clear up and occur again within a few days
- arthritic pain persists for more than 10 days, or redness is present or in conditions affecting children under 12 years of age

PREGNANCY OR BREAST FEEDING

If pregnant or breast-feeding, ask a health professional before use.

Keep out of reach of children.

If swallowed, get medical help or contact a Poison Control Center right away.

Directions

- adults and children 12 years of age and older: rub a thin film over affected area not more than 3 to 4 times daily
- children under 2 years of age: consult a physician
- wash hands after use with cool water

Other information

- store at 20–25ºC (68–77ºF)
- store in a cool dry place away from direct sunlight

Inactive Ingredients

Aloe Barbadensis Leaf Extract, Boswellia Serrata Extract (as B-NHIBITX™), Camphor, Carbomer, Dimethyl Sulfone (as OptiMSM®), FD&C Yellow #5, FD&C Blue #1, Glucosamine HCl, Ilex Paraguariensis Leaf Extract, Isopropyl Alcohol, Methylparaben, Tetrahydrodiferuloylmethane,
Tocopheryl Acetate (Vitamin E Acetate), Triethanolamine, Water.